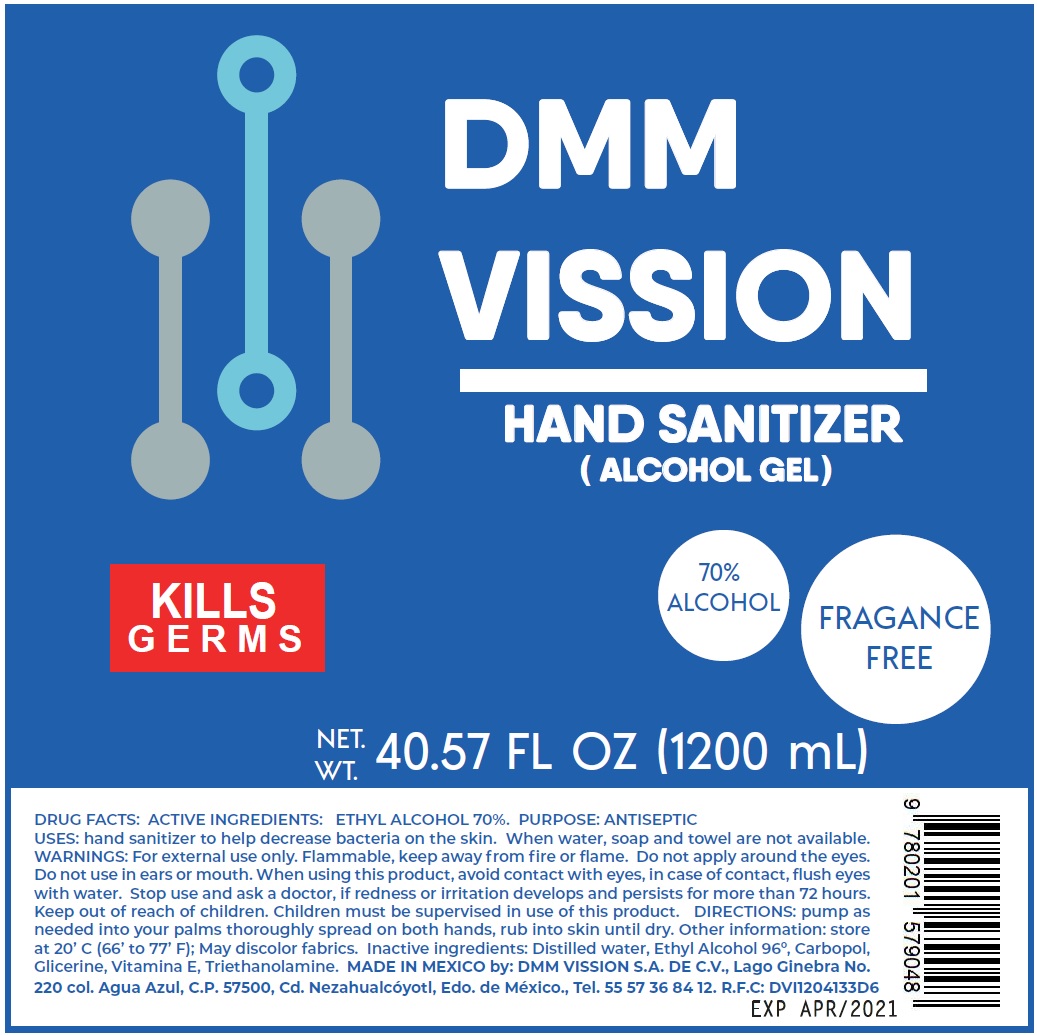 DRUG LABEL: DMM Vission Hand Sanitizer Alcohol
NDC: 75799-000 | Form: GEL
Manufacturer: DMM Vission, S.A. de C.V.
Category: otc | Type: HUMAN OTC DRUG LABEL
Date: 20200513

ACTIVE INGREDIENTS: ALCOHOL 0.7 mL/1 mL
INACTIVE INGREDIENTS: WATER; CARBOMER HOMOPOLYMER, UNSPECIFIED TYPE; GLYCERIN; .ALPHA.-TOCOPHEROL; TROLAMINE

DMM Vission Hand Sanitizer Alcohol Gel

ACTIVE INGREDIENTS:

ETHYL ALCOHOL 70%

PURPOSE:

ANTISEPTIC

USES:

hand sanitizer to help decrease bacteria on the skin. When water, soap and towel are not available.

WARNINGS:

For external use only. Flammable, keep away from fire or flame.

DO NOT USE

Do not apply around the eyes. Do not use in ears or mouth. When using this product, avoid contact with eyes, in case of contact, flush eyes with water.

When using this product

keep out of eyes, ears, and mouth. In case of contact with eyes, rinse eyes thoroughly with water.

Stop use and ask a doctor, if redness or irritation develops and persists for more than 72 hours.

Keep out of reach of children. Children must be supervised in use of this product.

DOSAGE AND ADMINISTRATION

DIRECTIONS: pump as needed into your palms thoroughly spread on both hands, rub into skin until dry.

Other information: store at 20’ C (66’ to 77’ F); May discolor fabrics.

INACTIVE INGREDIENT

Inactive ingredients: Distilled water, Ethyl Alcohol 96º, Carbopol, Glicerine, Vitamina E, Triethanolamine.